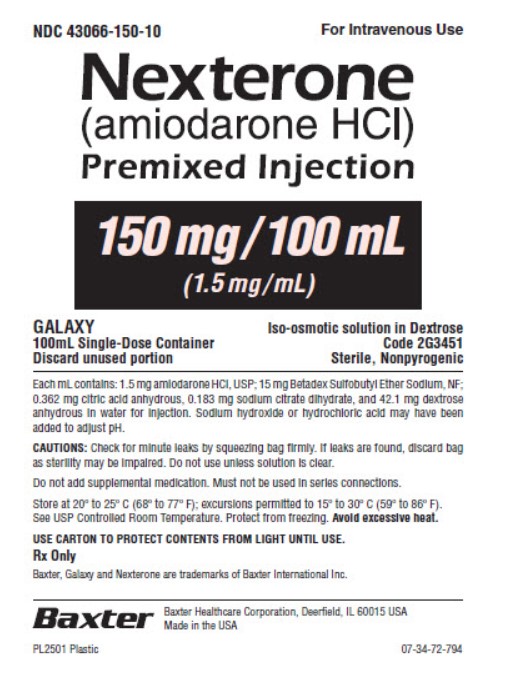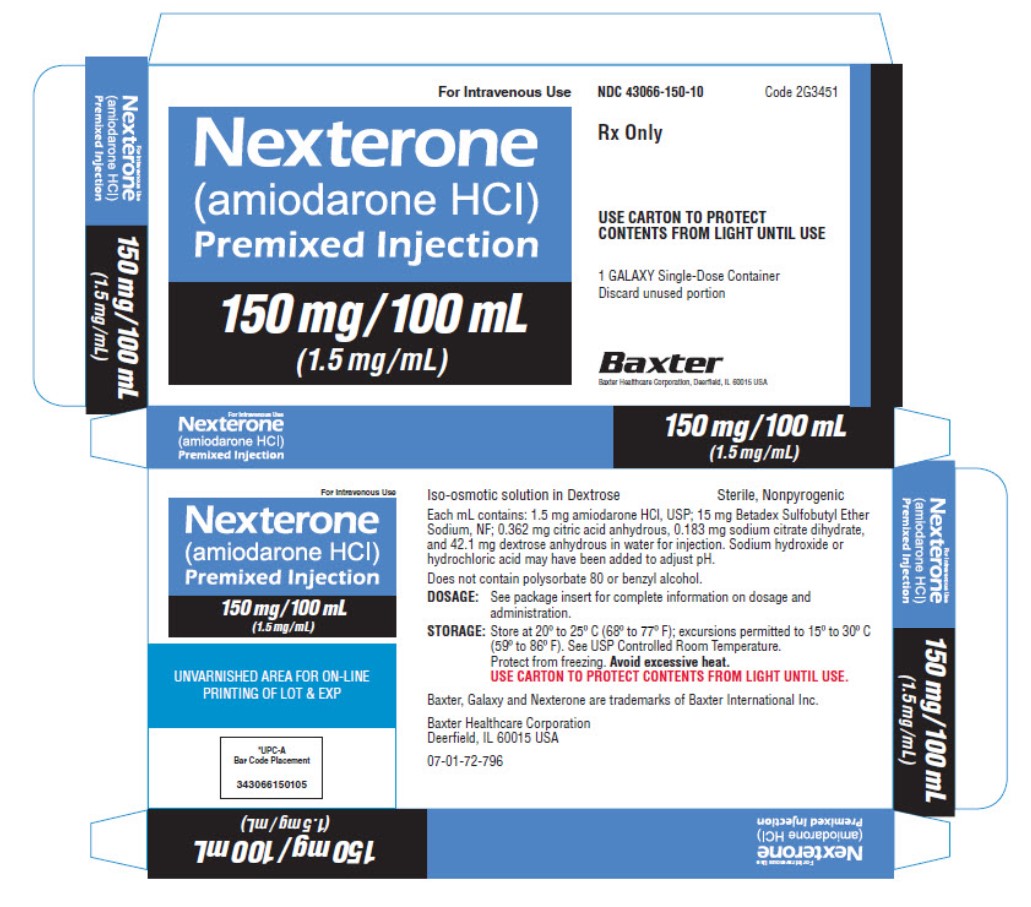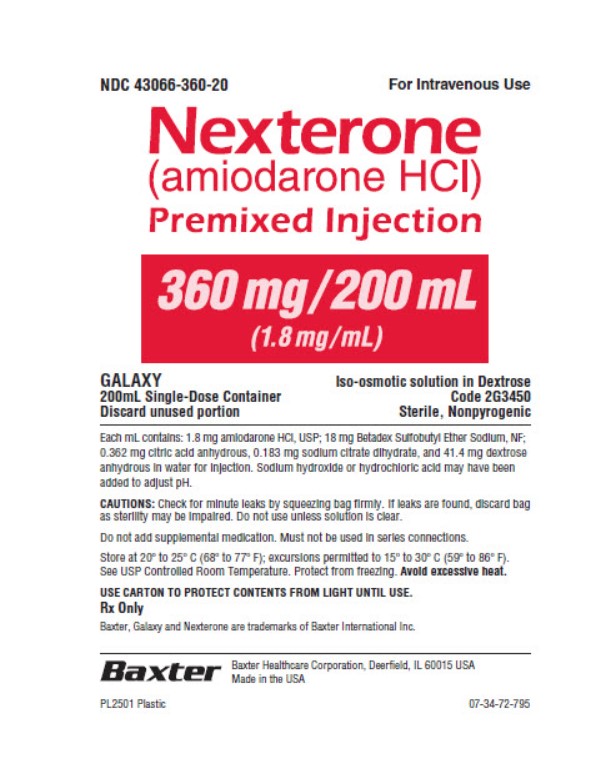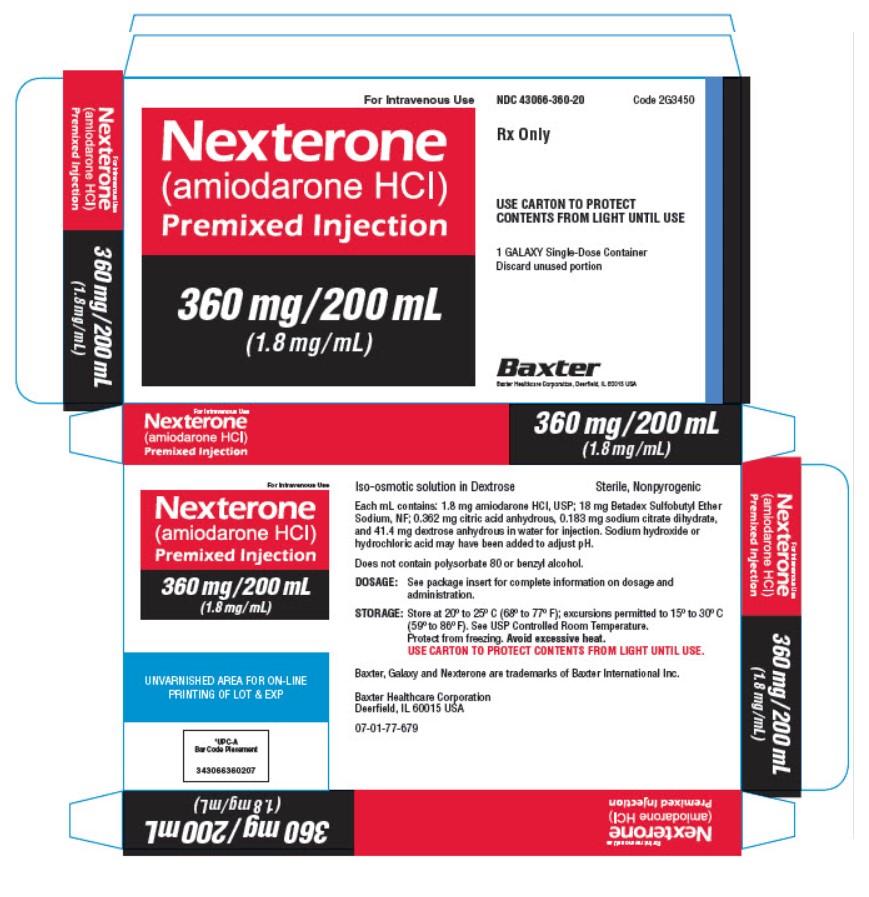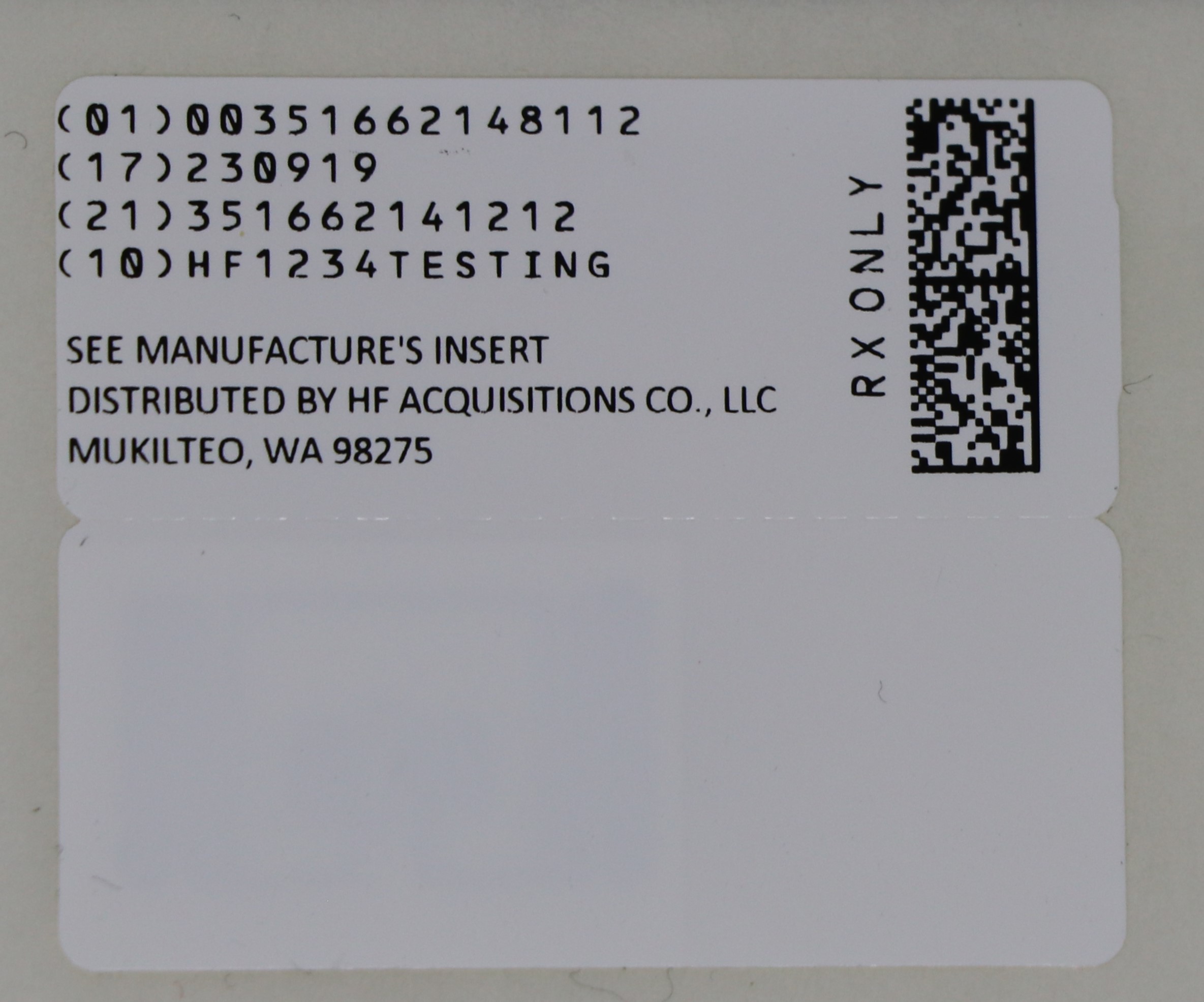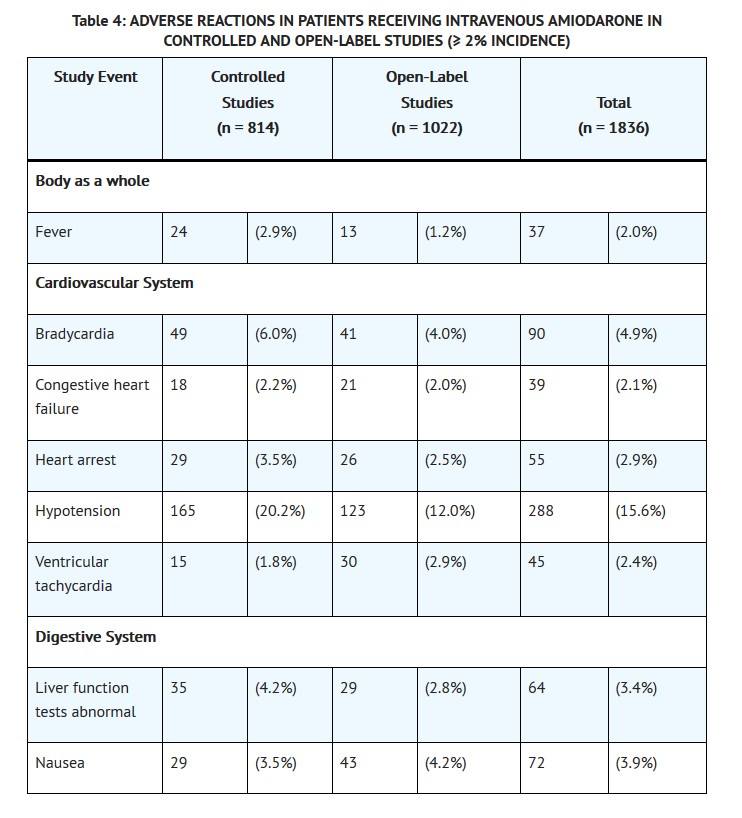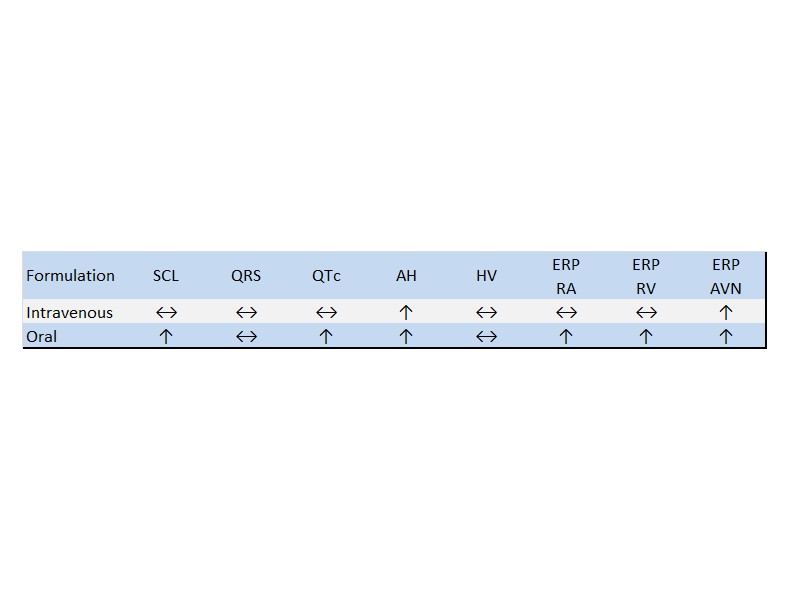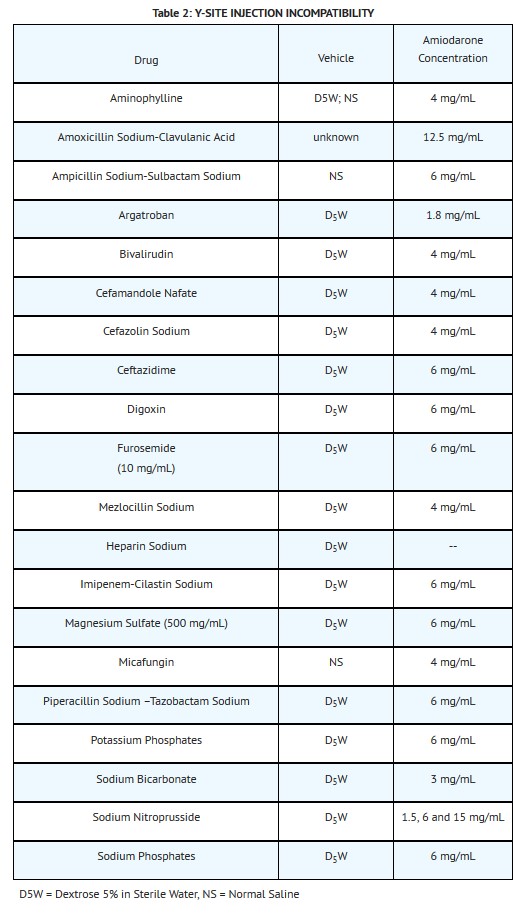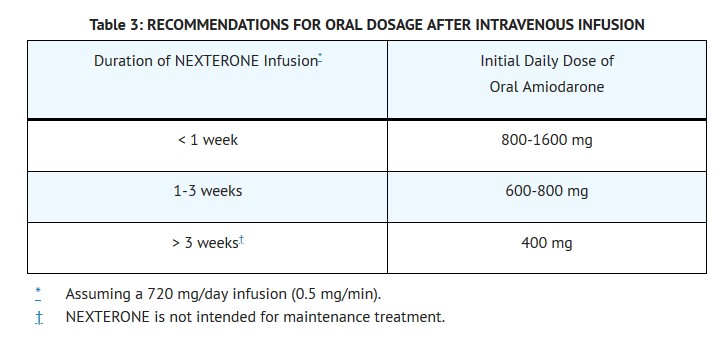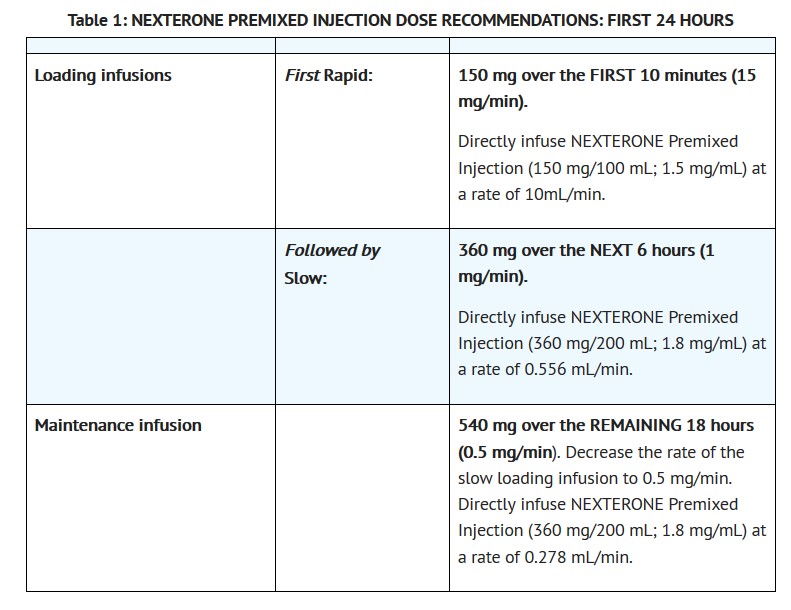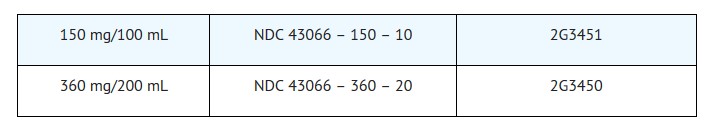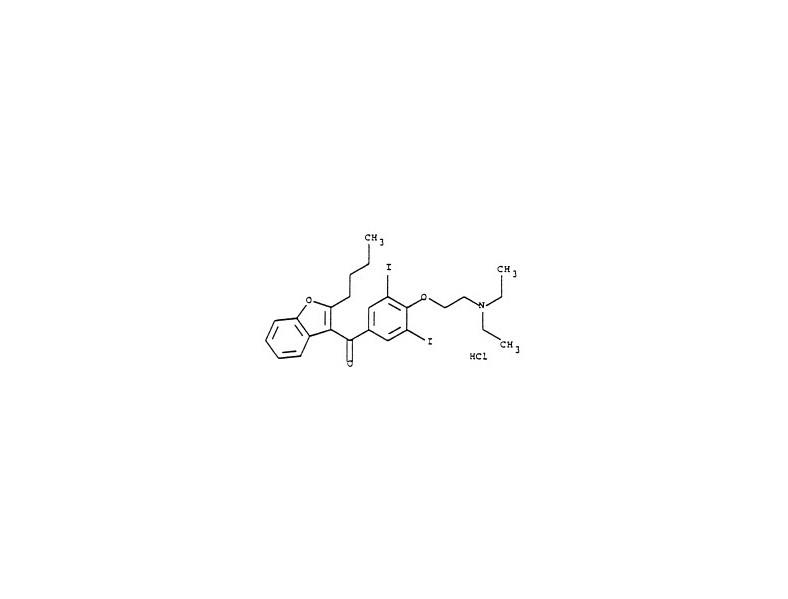 DRUG LABEL: NEXTERONE (AMIODARONE HCI)
NDC: 51662-1481 | Form: INJECTION, SOLUTION
Manufacturer: HF Acquisition Co LLC, DBA HealthFirst
Category: prescription | Type: HUMAN PRESCRIPTION DRUG LABEL
Date: 20240219

ACTIVE INGREDIENTS: AMIODARONE HYDROCHLORIDE 1.8 mg/1 mL
INACTIVE INGREDIENTS: BETADEX SULFOBUTYL ETHER SODIUM 18 mg/1 mL; ANHYDROUS CITRIC ACID 0.362 mg/1 mL; TRISODIUM CITRATE DIHYDRATE 0.183 mg/1 mL; HYDROCHLORIC ACID; ANHYDROUS DEXTROSE 41.4 mg/1 mL; SODIUM HYDROXIDE; WATER

NEXTERONE (AMIODARONE HCI) PREMIXED INJECTION

HIGHLIGHTS OF PRESCRIBING INFORMATION

These highlights do not include all the information needed to use NEXTERONE safely and effectively. See full prescribing information for NEXTERONE.
NEXTERONE (amiodarone HCl) Premixed Injection for intravenous use
Initial U.S. Approval: 1985

INDICATIONS AND USAGE

NEXTERONE is an antiarrhythmic agent indicated for initiation of treatment and prophylaxis of frequently recurring ventricular fibrillation (VF) and hemodynamically unstable ventricular tachycardia (VT) in patients refractory to other therapy. (1)

DOSAGE AND ADMINISTRATION

•
The recommended starting dose is about 1000 mg over the first 24 hours of therapy, delivered by the following infusion regimen (2):

o
Initial Load: 150 mg in 100 mL infused over 10 minutes
o
Followed by: 1 mg/min for 6 hours
o
Followed by: 0.5 mg/min thereafter

•
For breakthrough episodes of VF or hemodynamically unstable VT , repeat the Initial Load (2)

DOSAGE FORMS AND STRENGTHS

Injection, 1.5 mg/mL (150 mg/100 mL) Premixed in Dextrose (3)

Injection, 1.8 mg/mL (360 mg/200 mL) Premixed in Dextrose (3)

CONTRAINDICATIONS

NEXTERONE is contraindicated in patients with (4):

•
Known hypersensitivity to any of the components of NEXTERONE, including iodine
•
Cardiogenic shock
•
Marked sinus bradycardia
•
Second- or third-degree atrio-ventricular (AV) block unless a functioning pacemaker is available.

WARNINGS AND PRECAUTIONS

•
Hypotension: Slow the infusion; as needed, add vasopressor drugs, positive inotropic agents, and volume expansion. (5-5.1)
•
Bradycardia and AV block: Slow the infusion or discontinue. (5-5.2)

ADVERSE REACTIONS

•
The most common adverse reactions (1-2%) leading to discontinuation of intravenous amiodarone therapy are hypotension, asystole/cardiac arrest/pulseless electrical activity, VT, and cardiogenic shock. (6)
•
Other important adverse reactions are torsade de pointes, congestive heart failure, and liver function test abnormalities. (6)

To report SUSPECTED ADVERSE REACTIONS, contact Baxter Healthcare at 1-866-888-2472 or FDA at 1-800-FDA-1088 or www.fda.gov/medwatch.

DRUG INTERACTIONS

•
Amiodarone is a substrate for CYP3A and CYP2C8, so inhibitors and inducers affect amiodarone exposure (7)
•
Amiodarone inhibits p-glycoprotein and CYP1A2, CYP2C9, CYP2D6, and CYP3A, increasing exposure to other drugs (7)

USE IN SPECIFIC POPULATIONS

•
Pregnancy: Use NEXTERONE during pregnancy only if the potential benefit to the mother justifies the risk to the fetus (8-8.1).
•
Nursing mothers: Advise mothers to discontinue breast feeding (8-8.3).
•
Pediatric use: Safety and efficacy have not been established (8-8.4).

See 17 for PATIENT COUNSELING INFORMATION.

Revised: 11/2016

1 INDICATIONS & USAGE

NEXTERONE is indicated for initiation of treatment and prophylaxis of frequently recurring ventricular fibrillation (VF) and hemodynamically unstable ventricular tachycardia (VT) in patients refractory to other therapy. NEXTERONE also can be used to treat patients with VT/VF for whom oral amiodarone is indicated, but who are unable to take oral medication. During or after treatment with NEXTERONE, patients may be transferred to oral amiodarone therapy [see Dosage and Administration (2)].

Use NEXTERONE for acute treatment until the patient's ventricular arrhythmias are stabilized. Most patients will require this therapy for 48 to 96 hours, but NEXTERONE may be safely administered for longer periods if necessary.

2 DOSAGE & ADMINISTRATION

Amiodarone shows considerable interindividual variation in response. Although a starting dose adequate to suppress life-threatening arrhythmias is needed, close monitoring with adjustment of dose is essential. The recommended starting dose of NEXTERONE is about 1000 mg over the first 24 hours of therapy, delivered by the following infusion regimen:

After the first 24 hours, continue the maintenance infusion rate of 0.5 mg/min (720 mg per 24 hours) by directly infusing NEXTERONE Premixed Injection (360 mg/200 mL; 1.8 mg/mL) at a rate of 0.278 mL/min. The rate of the maintenance infusion may be increased to achieve effective arrhythmia suppression.

In the event of breakthrough episodes of VF or hemodynamically unstable VT, use 150 mg supplemental infusions of NEXTERONE (infused over 10 minutes to minimize the potential for hypotension).

The first 24-hour dose may be individualized for each patient; however, in controlled clinical trials, mean daily doses above 2100 mg were associated with an increased risk of hypotension. Do not exceed an initial infusion rate of 30 mg/min.

Based on the experience from clinical studies of intravenous amiodarone, a maintenance infusion of up to 0.5 mg/min can be continued for 2 to 3 weeks regardless of the patient's age, renal function, or left ventricular function. There has been limited experience in patients receiving intravenous amiodarone for longer than 3 weeks.

Administer NEXTERONE, whenever possible, through a central venous catheter dedicated to that purpose. Use an in-line filter during administration.

Intravenous amiodarone loading infusions at much higher concentrations and rates of infusion much faster than recommended have resulted in hepatocellular necrosis and acute renal failure, leading to death [see Warnings and Precautions (5-5.3)].

Intravenous amiodarone concentrations greater than 3 mg/mL have been associated with a high incidence of peripheral vein phlebitis; however, concentrations of 2.5 mg/mL or less appear to be less irritating. Therefore, for infusions longer than 1 hour, do not exceed NEXTERONE concentrations of 2 mg/mL, unless a central venous catheter is used [see Adverse Reactions (6-6.2)].

NEXTERONE Premixed Injection is available in GALAXY containers as a single-use, ready-to-use, iso-osmotic solution in dextrose for intravenous administration. No further dilution is required. NEXTERONE Premixed Injection should not be combined with any product in the same intravenous line or premixed container. Do not add supplemental medication. Protect from light until ready to use.

NEXTERONE does not need to be protected from light during administration.

Since the premixed container is for single-use only, any unused portion should be discarded.

NOTE: Inspect parenteral drug products for particulate matter and discoloration prior to administration, whenever solution and container permit, solution should be clear. Visually inspect the container. If the administration port protector is damaged, detached or not present, discard the container as the solution path sterility may be compromised. Check for minute leaks prior to use by squeezing the bag firmly. If leaks are detected, discard solution as sterility may be impaired.

CAUTION: Do not use plastic containers in series connections. Such use could result in air embolism due to residual air being drawn from the primary container before the administration of the fluid from the secondary container is complete.

Preparation of NEXTERONE Premixed Injection for administration:

1.
Suspend container from eyelet support.
2.
Remove protector from outlet port at bottom of container.
3.
Attach administration set. Refer to complete directions accompanying set.

Admixture Incompatibility
Amiodarone in D5W Injection forms precipitates with the drugs shown in Table 2. If co-administration of the following drugs is necessary, use separate intravenous administration lines.

Intravenous to Oral Transition
Patients whose arrhythmias have been suppressed by NEXTERONE may be switched to oral amiodarone. The optimal dose for changing from intravenous to oral administration of amiodarone will depend on the dose of NEXTERONE already administered, as well as the bioavailability of oral amiodarone. When changing to oral amiodarone therapy, clinical monitoring is recommended, particularly for elderly patients. See package insert for oral amiodarone.

Since grapefruit juice is known to inhibit CYP3A-mediated metabolism of oral amiodarone in the intestinal mucosa, resulting in increased plasma levels of amiodarone, do not drink grapefruit juice during treatment with oral amiodarone [see Drug Interactions (7)].

Table 3 provides suggested doses of oral amiodarone to be initiated after varying durations of NEXTERONE administration. These recommendations are made on the basis of a similar total body amount of amiodarone delivered by the intravenous and oral routes, based on 50% bioavailability of oral amiodarone.

3 DOSAGE FORMS & STRENGTHS

Injection, 1.5 mg/mL (150 mg/100 mL) Premixed in Dextrose

Injection, 1.8 mg/mL (360 mg/200 mL) Premixed in Dextrose

4 CONTRAINDICATIONS

NEXTERONE is contraindicated in patients with:

•
Known hypersensitivity to any of the components of NEXTERONE Premixed Injection, including iodine. Hypersensitivity reactions may involve rash, angioedema, cutaneous/mucosal hemorrhage (bleeding), fever, arthralgias (joint pains), eosinophilia (abnormal blood counts), uritcaria (hives), thrombotic thrombocytopenic purpura, or severe periarteritis (inflammation around blood vessels).
•
Cardiogenic shock.
•
Marked sinus bradycardia.
•
Second- or third-degree atrio-ventricular (AV) block unless a functioning pacemaker is available.

5 WARNINGS AND PRECAUTIONS

NEXTERONE should be administered only by physicians who are experienced in the treatment of life-threatening arrhythmias, who are thoroughly familiar with the risks and benefits of amiodarone therapy, and who have access to facilities adequate for monitoring the effectiveness and side effects of treatment.

Because of the long half-life of amiodarone and its metabolite desethylamiodarone, the potential for adverse reactions or interactions, as well as observed adverse effects, can persist following amiodarone withdrawal.

5.1 Hypotension

Hypotension is the most common adverse reaction seen with intravenous amiodarone. In clinical trials, treatment-emergent, drug-related hypotension was reported as an adverse effect in 288 (16%) of 1836 patients treated with intravenous amiodarone. Clinically significant hypotension during infusions was seen most often in the first several hours of treatment and was not dose related, but appeared to be related to the rate of infusion. Hypotension necessitating alterations in intravenous amiodarone therapy was reported in 3% of patients, with permanent discontinuation required in less than 2% of patients.

Treat hypotension initially by slowing the infusion; additional standard therapy may be needed, including the following: vasopressor drugs, positive inotropic agents, and volume expansion. Monitor the initial rate of infusion closely and do not exceed the recommended rate [see Dosage and Administration (2)].

In some cases, hypotension may be refractory and result in a fatal outcome [see Adverse Reactions (6-6.2)].

5.2 Bradycardia and Atrio-ventricular Block

In 90 (4.9%) of 1836 patients in clinical trials, drug-related bradycardia that was not dose-related occurred while they were receiving intravenous amiodarone for life-threatening VT/VF. Treat bradycardia by slowing the infusion rate or discontinuing NEXTERONE. In some patients, inserting a pacemaker is required. Despite such measures, bradycardia was progressive and terminal in 1 patient during the controlled trials. Treat patients with a known predisposition to bradycardia or AV block with NEXTERONE in a setting where a temporary pacemaker is available.

5.3 Hepatic Injury

Elevations of blood hepatic enzyme values [alanine aminotransferase (ALT), aspartate aminotransferase (AST), and gamma-glutamyl transferase (GGT)] are commonly seen in patients with immediately life-threatening VT/VF. Interpreting elevated AST activity can be difficult because the values may be elevated in patients who have had recent myocardial infarction, congestive heart failure, or multiple electrical defibrillations. Approximately 54% of patients receiving intravenous amiodarone in clinical studies had baseline liver enzyme elevations, and 13% had clinically significant elevations. In 81% of patients with both baseline and on-therapy data available, the liver enzyme elevations either improved during therapy or remained at baseline levels. Baseline abnormalities in hepatic enzymes are not a contraindication to treatment. Elevated bilirubin levels have been reported in patients administered intravenous amiodarone.

Acute, centrolobular confluent hepatocellular necrosis leading to hepatic coma, acute renal failure, and death has been associated with the administration of intravenous amiodarone [see Dosage and Administration (2)].

In patients with life-threatening arrhythmias, the potential risk of hepatic injury should be weighed against the potential benefit of NEXTERONE therapy. Carefully monitor patients receiving NEXTERONE for evidence of progressive hepatic injury. In such cases, consider reducing the rate of administration or withdrawing NEXTERONE.

5.4 Proarrhythmia

Like all antiarrhythmic agents, NEXTERONE may cause a worsening of existing arrhythmias or precipitate a new arrhythmia, sometimes leading to fatal outcomes [see Adverse Reactions (6-6.2)]. Proarrhythmia, primarily torsade de pointes (TdP), has been associated with prolongation, by intravenous amiodarone, of the QTc interval to 500 ms or greater. Although QTc prolongation occurred frequently in patients receiving intravenous amiodarone, TdP or new-onset VF occurred infrequently (less than 2%). Monitor patients for QTc prolongation during infusion with NEXTERONE. Reserve the combination of amiodarone with other antiarrhythmic therapies that prolong the QTc to patients with life-threatening ventricular arrhythmias who are incompletely responsive to a single agent.

Correct hypokalemia, hypomagnesemia or hypocalcemia whenever possible before initiating treatment with NEXTERONE, as these disorders can exaggerate the degree of QTc prolongation and increase the potential for TdP. Give special attention to electrolyte and acid-base balance in patients experiencing severe or prolonged diarrhea or in patients receiving concomitant diuretics and laxatives.

Amiodarone causes thyroid dysfunction in some patients, which may lead to potentially fatal breakthrough or exacerbated arrhythmias.

5.5 Pulmonary Injury

Early-onset Pulmonary Toxicity

There have been postmarketing reports of acute-onset (days to weeks) pulmonary injury in patients treated with intravenous amiodarone. Findings have included pulmonary infiltrates and masses on X-ray, bronchospasm, wheezing, fever, dyspnea, cough, hemoptysis, and hypoxia. Some cases have progressed to respiratory failure or death.

ARDS

Two percent (2%) of patients were reported to have adult respiratory distress syndrome (ARDS) during clinical studies involving 48 hours of therapy.

Pulmonary Fibrosis

There have been reports of early development of pulmonary fibrosis (within 1 to 3 months) following initiation of amiodarone treatment. Only 1 of more than 1000 patients treated with intravenous amiodarone in clinical studies developed pulmonary fibrosis. In that patient, the condition was diagnosed 3 months after treatment with intravenous amiodarone, during which time the patient received oral amiodarone. Pulmonary toxicity is a well-recognized complication of long-term amiodarone use (see package insert for oral amiodarone).

5.6 Loss of Vision

Cases of optic neuropathy and optic neuritis, usually resulting in visual impairment, have been reported in patients treated with oral amiodarone or intravenous amiodarone. In some cases, visual impairment has progressed to permanent blindness. Optic neuropathy and neuritis may occur at any time following initiation of therapy. A causal relationship to the drug has not been clearly established. Perform an ophthalmic examination if symptoms of visual impairment appear, such as changes in visual acuity and decreases in peripheral vision. Re-evaluate the necessity of amiodarone therapy if optic neuropathy or neuritis is suspected. Perform regular ophthalmic examination, including fundoscopy and slit-lamp examination, during administration of NEXTERONE.

5.7 Thyroid Abnormalities

Amiodarone inhibits peripheral conversion of thyroxine (T4) to triiodothyronine (T3) and may cause increased T4 levels, decreased T3 levels, and increased levels of inactive reverse T3 (rT3) in clinically euthyroid patients. Amiodarone is also a potential source of large amounts of inorganic iodine and can cause either hypothyroidism or hyperthyroidism. Evaluate thyroid function prior to treatment and periodically thereafter, particularly in elderly patients, and in any patient with a history of thyroid nodules, goiter, or other thyroid dysfunction. Because of the slow elimination of amiodarone and its metabolites, high plasma iodide levels, altered thyroid function, and abnormal thyroid-function tests may persist for several weeks or even months following NEXTERONE withdrawal.

There have been postmarketing reports of thyroid nodules/thyroid cancer in patients treated with amiodarone. In some instances hyperthyroidism was also present.

Hyperthyroidism and Thyrotoxicosis

Amiodarone causes hyperthyroidism in about 2% of patients. Thyrotoxicosis and arrhythmia with fatal outcome has been reported in the presence of pre-existing hyperthyroidism even following a single intravenous amiodarone dose. Consider the possibility of hyperthyroidism if any new signs of arrhythmia appear.

Hyperthyroidism may result from iodine load (type 1 amiodarone-induced thyrotoxicosis [type 1 AIT]; in particular in patients with underlying autonomous thyroid nodules or latent Grave’s disease). Hyperthyroidism may also result from direct amiodarone-induced destructive thyroiditis that occurs in individuals with no underlying thyroid disease (type 2 AIT), resulting in the release of preformed thyroid hormone into the bloodstream from damaged thyroid follicular epithelium. Mixed forms of hyperthyroidism as a result of both pathogenic mechanisms (excessive thyroid hormone production and thyroid destruction) can also occur. The risk of hyperthyroidism may be higher among patients with prior inadequate dietary iodine intake.

Identify hyperthyroidism by relevant clinical signs and symptoms, subnormal serum levels of thyroid stimulating hormone (TSH), abnormally elevated serum free T4, and elevated or normal serum T3. Since arrhythmia breakthroughs may accompany amiodarone-induced hyperthyroidism, aggressive medical treatment is indicated, including, if possible, dose reduction or withdrawal of amiodarone. Amiodarone hyperthyroidism may be followed by a transient period of hypothyroidism.

The institution of antithyroid drugs, β-adrenergic blockers or temporary corticosteroid therapy may be necessary. The action of antithyroid drugs may be especially delayed in amiodarone-induced thyrotoxicosis because of substantial quantities of preformed thyroid hormones stored in the gland. Radioactive iodine therapy is not recommended because of the low radioiodine uptake associated with amiodarone-induced hyperthyroidism.

When aggressive treatment of amiodarone-induced thyrotoxicosis has failed or amiodarone cannot be discontinued because it is the only drug effective against the resistant arrhythmia, surgical management may be an option. Experience with thyroidectomy as a treatment for amiodarone-induced thyrotoxicosis is limited, and this form of therapy could induce thyroid storm. Therefore, surgical and anesthetic management require careful planning.

Hypothyroidism

Hypothyroidism has been reported in 2 to 10% of patients receiving amiodarone and may be primary or subsequent to resolution of preceding amiodarone-induced hyperthyroidism. This condition may be identified by clinical symptoms and elevated serum TSH levels. Cases of severe hypothyroidism and myxedema coma, sometimes fatal, have been reported in association with amiodarone therapy. In some clinically hypothyroid amiodarone-treated patients, free thyroxine index values may be normal. Manage hypothyroidism by reducing the dose of or discontinuing NEXTERONE and considering the need for thyroid hormone supplement.

5.8 Neonatal Injury

Amiodarone can cause fetal harm when administered to a pregnant woman. Fetal exposure may increase the potential for adverse experiences including cardiac, thyroid, neurodevelopmental, neurological and growth effects in neonate. Inform the patient of the potential hazard to the fetus if NEXTERONE is administered during pregnancy or if the patient becomes pregnant while taking NEXTERONE [See Pregnancy (8-8.1)].

5.9 Exaggerated Effects of Perisurgical Therapy

Perform close perioperative monitoring in patients undergoing general anesthesia who are on amiodarone therapy as they may be more sensitive to the myocardial depressant and conduction defects of halogenated inhalational anesthetics.

5.10 Interference with Corneal Refractive Laser Surgery

Advise patients that most manufacturers of corneal refractive laser surgery devices contraindicate corneal refractive laser surgery in patients taking amiodarone.

5.11 Hypersensitivity Reactions

Anaphylactic/anaphylactoid reactions have been reported with intravenous amiodarone including shock (sometimes fatal), cardiac arrest, and the following manifestations: hypotension, tachycardia, hypoxia, cyanosis, rash, flushing, hyperhidrosis and cold sweat. Since NEXTERONE contains dextrose, patients with allergy to corn or corn products are at risk for allergic reaction.

6 ADVERSE REACTIONS

The following adverse reactions are described in Warnings and Precautions: hypotension, rhythm disturbances, hepatic injury, pulmonary injury, thyroid injury, hypersensitivity.

6.1 Clinical Trials Experience

Because clinical trials are conducted under widely varying conditions, adverse reaction rates observed in the clinical trials of a drug cannot be directly compared to rates in the clinical trials of another drug and may not reflect the rates observed in practice.

In a total of 1836 patients in controlled and uncontrolled clinical trials, 14% of patients received intravenous amiodarone for at least one week, 5% received it for at least 2 weeks, 2% received it for at least 3 weeks, and 1% received it for more than 3 weeks, without an increased incidence of severe adverse reactions. The mean duration of therapy in these studies was 5.6 days; median exposure was 3.7 days.

The most important adverse reactions were hypotension, asystole/cardiac arrest/pulseless electrical activity (PEA), cardiogenic shock, congestive heart failure, bradycardia, liver function test abnormalities, VT, and AV block. Overall, treatment was discontinued for about 9% of the patients because of adverse reactions. The most common adverse reactions leading to discontinuation of intravenous amiodarone therapy were hypotension (1.6%), asystole/cardiac arrest/PEA (1.2%), VT (1.1%), and cardiogenic shock (1%).

Table 4 lists the most common (incidence ≥2%) adverse reactions during intravenous amiodarone therapy considered at least possibly drug-related. These data were collected in clinical trials involving 1836 patients with life-threatening VT/VF. Data from all assigned treatment groups are pooled because none of the adverse reactions appeared to be dose-related.

Other adverse reactions reported in less than 2% of patients receiving intravenous amiodarone in controlled and uncontrolled studies included the following: abnormal kidney function, atrial fibrillation, diarrhea, increased ALT, increased AST, lung edema, nodal arrhythmia, prolonged QT interval, atrioventricular block, respiratory disorder, shock, sinus bradycardia, Stevens-Johnson syndrome, thrombocytopenia, VF, and vomiting.

6.2 Post-Marketing Experience

The following adverse reactions have been reported in the post-marketing experience during or in close temporal relationship to intravenous amiodarone administration. Because these reactions are reported voluntarily from a population of uncertain size, it is not always possible to reliably estimate their frequency or establish a causal relationship to drug exposure.

Blood and Lymphatic System Disorders: pancytopenia, neutropenia, hemolytic anemia, aplastic anemia, thrombocytopenia, and granulocytosis.

Cardiac Disorders: sinus node dysfunction (sinus arrest, sinoatrial block), intraventricular conduction disorders including bundle branch block and infra-HIS block, bradycardia (sometimes fatal), ventricular extrasystoles, and antegrade conduction via an accessory pathway.

Endocrine Disorders: syndrome of inappropriate antidiuretic hormone secretion (SIADH).

Eye Disorders: visual field defect and blurred vision.

Gastrointestinal Disorders: pancreatitis.

General Disorders and Administration Site Conditions: infusion site reactions, including thombosis, phlebitis, thrombophlebitis, cellulitis, pain, induration, edema, inflammation, urticaria, pruritus, erythema, pigment changes, hypoesthesia, skin sloughing, extravasation possibly leading to venous/infusion site necrosis, intravascular amiodarone deposition/mass (developed in the superior vena cava around acentral venous catheter after long – term [28 days] amiodarone therapy administered through a central line), and granuloma.

Hepatobiliary Disorders: cholestasis, cirrhosis, jaundice, alkaline phosphatase and blood lactate dehydrogenase increase.

Musculoskeletal and Connective Tissue Disorders: myopathy, muscle weakness, rhabdomyolysis, muscle spasms, and back pain.

Neoplasms benign, malignant and unspecified (incl cysts and polyps) Disorders: thyroid nodules/thyroid cancer.

Nervous System Disorders: intracranial pressure increased, pseudotumor cerebri, tremor, dizziness and hypoesthesia.

Psychiatric Disorders: confusional state, hallucination, disorientation, and delirium.

Renal and Urinary Disorders: acute renal failure (sometimes fatal), renal impairment, renal insufficiency, and blood creatinine increased.

Reproductive Disorders and Breast Disorders: Epididymitis

Respiratory, Thoracic and Mediastinal Disorders: interstitial pneumonitis, bronchiolitis obliterans organizing pneumonia (possibly fatal), pulmonary alveolar hemorrhage, pulmonary phospholipidoisis, pleural effusion, bronchospasm, dyspnea, cough, hemoptysis, wheezing, and hypoxia.

Skin and Subcutaneous Tissue Disorders: toxic epidermal necrolysis (sometimes fatal), Stevens-Johnson syndrome, exfoliative dermatitis, erythema multiforme, skin cancer, pruritus, angioedema, and urticaria.

Vascular Disorders: vasculitis and flushing.

7 DRUG INTERACTIONS

7.1 Pharmacodynamic Interactions

Drugs prolonging the QT interval: Co-administration of drugs prolonging the QT interval (such as class I and III antiarrhythmics, lithium, certain phenothiazines, tricyclic antidepressants, certain fluoroquinolone and macrolide antibiotics, azole antifungals, halogenated inhalation anesthetic agents) increases the risk of Torsade de Pointes. In general, avoid concomitant use of drugs that prolong the QT interval [see Warnings and Precautions (5-5.4)].

Drugs that slow heart rate: Concomitant use of drugs with depressant effects on the sinus and AV node (e.g., digoxin, beta blockers, verapamil, diltiazem, ivabradine, clonidine) can potentiate the electrophysiologic and hemodynamic effects of amiodarone, resulting in bradycardia, sinus arrest, and AV block. Monitor heart rate in patients on amiodarone and concomitant drugs that slow heart rate.

7.2 Pharmacokinetic Interactions

Effect of other drugs on amiodarone

Amiodarone is metabolized to the active metabolite desethylamiodarone (DEA) by the cytochrome P450 (CYP450) enzyme group, specifically CYP3A and CYP2C8. Amiodarone has the potential for interactions with drugs or substances that may be substrates, inhibitors or inducers of CYP450 enzymes (e.g., inhibitors such as protease inhibitors, grapefruit juice, certain fluoroquinolone and macrolide antibiotics, azole antifungals and inducers such as St. John’s Wort) or P-glycoprotein. In view of the long and variable half-life of amiodarone, potential for drug interactions exists not only with concomitant medication but also with drugs administered after discontinuation of amiodarone [see Clinical Pharmacology (12-12.3)].

Patients should avoid grapefruit juice beverages while taking amiodarone because exposure to amiodarone is significantly increased [see Clinical Pharmacology (12-12.3)].

Effect of amiodarone on other drugs

Amiodarone and DEA are inhibitors of P-glycoprotein and certain CYP450 enzymes, including CYP1A2, CYP2C9, CYP2D6 and CYP3A [see Clinical Pharmacology (12-12.3)].

Antiarrhythmics: The metabolism of quinidine, procainamide, flecainide can be inhibited by amiodarone. In general, initiate any added antiarrhythmic drug at a lower than usual dose and monitor the patient carefully. During transfer to oral amiodarone, reduce the dose levels of previously administered agents by 30 to 50% several days after the addition of oral amiodarone. Review the continued need for the other antiarrhythmic agent after the effects of amiodarone have been established, and attempt discontinuation [see Clinical Pharmacology (12-12.3)].

Digoxin: In patients receiving digoxin therapy, administration of oral amiodarone results in an increase in serum digoxin concentration. Reduce dose of digoxin by half or discontinue digoxin. If digitalis treatment is continued, monitor serum levels closely and observe patients for clinical evidence of toxicity [see Clinical Pharmacology (12-12.3)].

HMG-CoA Reductase Inhibitors: Limit the dose of simvastatin in patients on amiodarone to 20 mg daily. Limit the daily dose of lovastatin to 40 mg. Lower starting and maintenance doses of other CYP3A4 substrates (e.g., atorvastatin) may be required as amiodarone may increase the plasma concentration of these drugs.

Anticoagulants: Potentiation of warfarin-type (CYP2C9 and CYP3A substrate) anticoagulant response is almost always seen in patients receiving amiodarone and can result in serious or fatal bleeding. Since the concomitant administration of warfarin with amiodarone increases the INR by 100% after 3 to 4 days, reduce the dose of the anticoagulant by one-third to one-half, and monitor INR closely.

Cyclosporine (CYP3A substrate) administered in combination with oral amiodarone has been reported to produce persistently elevated plasma concentrations of cyclosporine resulting in elevated creatinine, despite reduction in dose of cyclosporine. Monitor cyclosporine drug levels and renal function in patients taking both drugs.

Increased steady-state levels of phenytoin during concomitant therapy with amiodarone have been reported. Monitor phenytoin levels in patients taking both drugs.

7.3 Serious Symptomatic Bradycardia When Co-administered with Ledipasvir/Sofosbuvir or with Sofosbuvir with Simeprevir

Postmarketing cases of symptomatic bradycardia, some requiring pacemaker insertion and at least one fatal, have been reported when ledipasvir/sofosbuvir or sofosbuvir with simeprevir were initiated in patients on amiodarone. Bradycardia generally occurred within hours to days, but in some cases up to 2 weeks after initiating antiviral treatment. Bradycardia generally resolved after discontinuation of antiviral treatment. The mechanism for this effect is unknown. Monitor heart rate in patients taking or recently discontinuing amiodarone when starting antiviral treatment.

8 USE IN SPECIFIC POPULATIONS

8.1 Pregnancy

Pregnancy Category D [see Warnings and Precautions (5-5.8)].

Teratogenic Effects

Amiodarone and desethylamiodarone cross the placenta.

Reported risks include:

•
neonatal bradycardia, QT prolongation, and periodic ventricular extrasystoles
•
neonatal hypothyroidism (with or without goiter) detected antenatally or in the newborn and reported even after a few days of exposure
•
neonatal hyperthyroxinemia
•
neurodevelopmental abnormalities independent of thyroid function, including speech delay and difficulties with written language and arithmetic, delayed motor development, and ataxia.
•
jerk nystagmus with synchronous head titubation
•
fetal growth retardation
•
premature birth

Amiodarone has caused a variety of adverse effects in animals.

Amiodarone was given intravenously to rabbits at dosages of 5, 10, or 25 mg/kg per day (about 0.1, 0.3, and 0.7 times human intravenous maintenance dose of 0.5 mg/min on a body surface area basis), during gestation days 8 to 16 (organogenesis). The incidence of maternal deaths increased with increasing dose and occurred in all treated groups and controls. Mean fetal weights were significantly decreased in the low and middle dose groups and embryotoxicity (as manifested by fewer full-term fetuses and increased resorptions) occurred at dosages of 10 mg/kg and above. There were no significant differences in the number of minor fetal abnormalities and no major fetal abnormalities were observed.

Amiodarone was administered by continuous intravenous infusion to rats at dosages of 25, 50, or 100 mg/kg per day (about 0.3, 0.7 and 1.3 times the human intravenous maintenance dose of 0.5 mg/min on a body surface area basis) during gestation days 8 to 16 (organogenesis). Maternal toxicity (manifest as reduced weight gain and food consumption) and embryotoxicity (manifest as increased resorptions, decreased live litter size and fetal body weights, and delayed sternal and metacarpal ossification) were observed in the 100 mg/kg group. The delayed ossification was reversible and related to decreased fetal weight. Fetal thyroid tissues appeared normal in all groups.

Nonteratogenic Effects

Very high concentrations of amiodarone and desethylamiodarone may be found in testes. An elevated follicle-stimulating hormone and luteinizing hormone levels, suggestive of testicular dysfunction, have been reported in men on long-term amiodarone treatment.

While planning pregnancy after discontinuation of amiodarone treatment, consider the long half-life of amiodarone and its metabolite DEA.

8.2 Labor and Delivery

It is not known whether the use of amiodarone during labor or delivery has any immediate or delayed adverse effects. Preclinical studies in rodents have not shown any effect on the duration of gestation or on parturition.

8.3 Nursing Mothers

Amiodarone and one of its major metabolites, desethylamiodarone (DEA), are excreted in human milk, suggesting that breast-feeding could expose the nursing infant to a significant dose of the drug. Nursing offspring of lactating rats administered amiodarone have demonstrated reduced viability and transient reduced body weight gains. The risk of exposing the infant to amiodarone and DEA must be weighed against the potential benefit of arrhythmia suppression in the mother. Advise the mother to discontinue nursing.

8.4 Pediatric Use

The safety and effectiveness of amiodarone in pediatric patients have not been established; therefore, the use of amiodarone in pediatric patients is not recommended. In a pediatric trial of 61 patients, aged 30 days to 15 years, hypotension (36%), bradycardia (20%), and AV block (15%) were common dose-related adverse reactions and were severe or life-threatening in some cases. Injection site reactions were seen in 5 (25%) of the 20 patients receiving intravenous amiodarone through a peripheral vein irrespective of dose regimen.

8.5 Geriatric Use

Clinical studies of amiodarone did not include sufficient numbers of subjects aged 65 and over to determine whether they respond differently from younger subjects. Other reported clinical experience has not identified differences in responses between the elderly and younger patients. Carefully consider dose selection in an elderly patient. In general, start at the low end of the dosing range in the elderly to reflect the greater frequency of decreased hepatic, renal, or cardiac function, and concomitant disease or other drug therapy.

10 OVERDOSAGE

There have been cases, some fatal, of amiodarone overdose. Effects of an inadvertent overdose of intravenous amiodarone include hypotension, cardiogenic shock, bradycardia, AV block, and hepatotoxicity. Treat hypotension and cardiogenic shock by slowing the infusion rate or with standard therapy: vasopressor drugs, positive inotropic agents, and volume expansion. Bradycardia and AV block may require temporary pacing. Monitor hepatic enzyme concentrations closely. Neither amiodarone nor DEA is dialyzable.

11 DESCRIPTION

NEXTERONE contains amiodarone HCl (C25H29I2NO3•HCl), a class III antiarrhythmic drug. Amiodarone HCl is (2-butyl-3-benzo-furanyl)[4-[2-(diethylamino)ethoxy]-3,5- diiodophenyl] methanone hydrochloride.

Amiodarone HCl has the following structural formula:

Amiodarone HCl is a white to slightly yellow crystalline powder, and is very slightly soluble in water. It has a molecular weight of 681.78 and contains 37.3% iodine by weight. NEXTERONE Premixed Injection is a sterile clear, colorless to slightly yellow solution visually free from particulates. NEXTERONE Premixed Injection is available as a ready-to-use, nonpyrogenic, iso-osmotic solution for intravenous administration in 100 mL GALAXY containers with 150 mg of amiodarone HCl, USP (1.5 mg/mL) in dextrose, and 200 mL GALAXY containers with 360 mg of amiodarone HCl, USP (1.8 mg/mL) in dextrose.

NEXTERONE Premixed Injection (150 mg/100 mL, 1.5 mg/mL):

Each mL contains 1.5 mg of amiodarone HCl, USP, 15 mg Betadex Sulfobutyl Ether Sodium, NF, 0.362 mg citric acid anhydrous, 0.183 mg sodium citrate dihydrate and 42.1 mg dextrose anhydrous in water for injection. Sodium hydroxide or hydrochloric acid may have been added to adjust pH.

NEXTERONE Premixed Injection (360 mg/200 mL, 1.8 mg/mL):

Each mL contains 1.8 mg of amiodarone HCl, USP, 18 mg Betadex Sulfobutyl Ether Sodium, NF, 0.362 mg citric acid anhydrous, 0.183 mg sodium citrate dihydrate and 41.4 mg dextrose anhydrous in water for injection. Sodium hydroxide or hydrochloric acid may have been added to adjust pH.

NEXTERONE does not contain polysorbate 80 or benzyl alcohol.

The GALAXY container is fabricated from a specially designed multilayered plastic (PL 2501). Solutions are in contact with the polyethylene layer of the container and can leach out certain chemical components of the plastic in very small amounts within the expiration period. The suitability and safety of the plastic have been confirmed in tests in animals according to the USP biological tests for plastic containers, as well as by tissue culture toxicity studies.

12 CLINICAL PHARMACOLOGY

12.1 Mechanism of Action

Amiodarone is generally considered a class III antiarrhythmic drug, but it possesses electrophysiologic characteristics of all four Vaughan Williams classes. Like class I drugs, amiodarone blocks sodium channels at rapid pacing frequencies, and like class II drugs, amiodarone exerts a noncompetitive antisympathetic action. One of its main effects, with prolonged administration, is to lengthen the cardiac action potential, a class III effect. The negative chronotropic effect of amiodarone in nodal tissues is similar to the effect of class IV drugs. In addition to blocking sodium channels, amiodarone blocks myocardial potassium channels, which contributes to slowing of conduction and prolongation of refractoriness. The antisympathetic action and the block of calcium and potassium channels are responsible for the negative dromotropic effects on the sinus node and for the slowing of conduction and prolongation of refractoriness in the atrioventricular (AV) node. Its vasodilatory action can decrease cardiac workload and consequently myocardial oxygen consumption.

Intravenous amiodarone administration prolongs intranodal conduction (Atrial-His, AH) and refractoriness of the atrioventricular node (ERP AVN), but has little or no effect on sinus cycle length (SCL), refractoriness of the right atrium and right ventricle (ERP RA and ERP RV), repolarization (QTc), intraventricular conduction (QRS), and infra-nodal conduction (His-ventricular, HV). A comparison of the electrophysiologic effects of intravenous amiodarone and oral amiodarone is shown in the table below.

At higher doses (>10 mg/kg) of intravenous amiodarone, prolongation of the ERP RV and modest prolongation of the QRS have been seen. These differences between oral and IV administration suggest that the initial acute effects of intravenous amiodarone may be predominately focused on the AV node, causing an intranodal conduction delay and increased nodal refractoriness due to slow channel blockade (class IV activity) and noncompetitive adrenergic antagonism (class II activity).

12.2 Pharmacodynamics

Intravenous amiodarone has been reported to produce negative inotropic and vasodilatory effects in animals and humans. In clinical studies of patients with refractory VF or hemodynamically unstable VT, treatment-emergent, drug-related hypotension occurred in 288 of 1836 patients (16%) treated with intravenous amiodarone. No correlations were seen between the baseline ejection fraction and the occurrence of clinically significant hypotension during infusion of intravenous amiodarone.

No data are available on the activity of DEA in humans, but in animals, it has significant electrophysiologic and antiarrhythmic effects generally similar to amiodarone itself. DEA's precise role and contribution to the antiarrhythmic activity of oral amiodarone are not certain. The development of maximal ventricular class III effects after oral amiodarone administration in humans correlates more closely with DEA accumulation over time than with amiodarone accumulation. On the other hand, after intravenous amiodarone administration, there is evidence of activity well before significant concentrations of DEA are attained [see Clinical Trials (14)].

12.3 Pharmacokinetics

Disposition:

Amiodarone exhibits complex disposition characteristics after intravenous administration. Peak serum concentrations after single 5 mg/kg 15-minute intravenous infusions in healthy subjects range between 5 and 41 mg/L. Peak concentrations after 10-minute infusions of 150 mg intravenous amiodarone in patients with ventricular fibrillation (VF) or hemodynamically unstable ventricular tachycardia (VT) range between 7 and 26 mg/L. Due to rapid distribution, serum concentrations decline to 10% of peak values within 30 to 45 minutes after the end of the infusion. In clinical trials, after 48 hours of continued infusions (125, 500 or 1000 mg/day) plus supplemental (150 mg) infusions (for recurrent arrhythmias), amiodarone mean serum concentrations between 0.7 to 1.4 mg/L were observed (n=260).

Metabolism:

N-desethylamiodarone (DEA) is the major active metabolite of amiodarone in humans. DEA serum concentrations above 0.05 mg/L are not usually seen until after several days of continuous infusion but with prolonged therapy reach approximately the same concentration as amiodarone. Amiodarone is metabolized to DEA by the cytochrome P450 (CYP450) enzyme group, specifically cytochrome P4503A (CYP3A) and CYP2C8. The CYP3A isoenzyme is present in both the liver and intestines. The highly variable systemic availability of oral amiodarone may be attributed potentially to large interindividual variability in CYP3A activity.

Distribution/Elimination:

From in vitro studies, the protein binding of amiodarone is >96%. Amiodarone and DEA cross the placenta and both appear in breast milk. Neither amiodarone nor DEA is dialyzable.

Amiodarone is eliminated primarily by hepatic metabolism and biliary excretion and there is negligible excretion of amiodarone or DEA in urine. In studies in healthy subjects following single intravenous administration (5 mg/kg of amiodarone over 15 min), the plasma concentration vs. time profile could be characterized by linear sum of four exponential terms with terminal elimination half-lives (t½) of 9 - 36 days for amiodarone and 9 - 30 days for DEA. The clearance of amiodarone and DEA ranged between 63 - 231 mL/hr/kg and 140 - 400 ml/h/kg, respectively. In clinical studies of 2 to 7 days, clearance of amiodarone after intravenous administration in patients with VT and VF ranged between 220 and 440 mL/hr/kg.

Special Populations:

Effect of Age: The pharmacokinetics of amiodarone and DEA are affected by age. Normal subjects over 65 years of age show lower clearances (about 100 mL/hr/kg) than younger subjects (about 150 mL/hr/kg) and an increase in t½ from about 20 to 47 days.

Effect of Gender: Pharmacokinetics of amiodarone and DEA are similar in males and females.

Renal Impairment: Renal disease does not influence the pharmacokinetics of amiodarone or DEA.

Hepatic Impairment: After a single dose of intravenous amiodarone to cirrhotic patients, significantly lower Cmax and average concentration values are seen for DEA, but mean amiodarone levels are unchanged.

Cardiac Disease: In patients with severe left ventricular dysfunction, the pharmacokinetics of amiodarone are not significantly altered but the terminal elimination t½ of DEA is prolonged.

Although no dosage adjustment for patients with renal, hepatic, or cardiac abnormalities has been defined during chronic treatment with oral amiodarone, close clinical monitoring is prudent for elderly patients and those with severe left ventricular dysfunction.

Exposure-Response:

There is no established relationship between drug concentration and therapeutic response for short-term intravenous use.

Drug Interactions:

Effect of other drugs on amiodarone:

Cimetidine inhibits CYP3A and can increase serum amiodarone levels.

Grapefruit juice given to healthy volunteers increased amiodarone AUC by 50% and Cmax by 84%, resulting in increased plasma levels of amiodarone.

Cholestyramine reduces enterohepatic circulation of amiodarone thereby increasing its elimination. This results in reduced amiodarone serum levels and half-life.

Effect of amiodarone on other drugs:

Amiodarone taken concomitantly with quinidine increases quinidine serum concentration by 33% after two days. Amiodarone taken concomitantly with procainamide for less than seven days increases plasma concentrations of procainamide and n-acetyl procainamide by 55% and 33%, respectively.

Loratadine, a non-sedating antihistaminic, is metabolized primarily by CYP3A and its metabolism can be inhibited by amiodarone.

Metabolism of lidocaine can be inhibited by amiodarone. Sinus bradycardia has been reported with oral amiodarone in combination with lidocaine (CYP3A substrate) given for local anesthesia. Seizure, associated with increased lidocaine concentrations, has been reported with concomitant administration of intravenous amiodarone.

Amiodarone can inhibit the metabolism of macrolide/ketolide antibiotics (except for azithromycin) and systemic azole antifungal drugs.

Amiodarone taken concomitantly with digoxin increases the serum digoxin concentration by 70% after one day.

Dextromethorphan is a substrate for both CYP2D6 and CYP3A. Amiodarone inhibits CYP2D6.Chronic (> 2 weeks) oral amiodarone administration impairs metabolism of dextromethorphan can lead to increased serum concentrations.

Dabigatran etexilate when taken concomitantly with oral amiodarone can result in elevated serum concentration of dabigatran.

Cyclophosphamide is a prodrug, metabolized by CYP450 including CYP3A to an active metabolite. The metabolism of cyclophosphamide may be inhibited by amiodarone.

Clopidogrel, an inactive thienopyridine prodrug, is metabolized in the liver by CYP3A to an active metabolite. A potential interaction between clopidogrel and amiodarone resulting in ineffective inhibition of platelet aggregation has been reported.

13 NONCLINICAL TOXICOLOGY

13.1 Carcinogenesis, Mutagenesis, Impairment of Fertility

No carcinogenicity studies were conducted with intravenous administration of amiodarone. However, oral amiodarone caused a statistically significant, dose-related increase in the incidence of thyroid tumors (follicular adenoma and carcinoma) in rats. The incidence of thyroid tumors in rats was greater than the incidence in controls even at the lowest dose level tested, i.e., 5 mg/kg/day (much less, on a body surface area basis, than the maximum recommended human maintenance dose of 600 mg/day).

Mutagenicity studies conducted with amiodarone HCl (Ames, micronucleus, and lysogenic induction tests) were negative.

No fertility studies were conducted with intravenous administration of amiodarone. However, in a study in which amiodarone HCl was orally administered to male and female rats, beginning 9 weeks prior to mating, reduced fertility was observed at a dose level of 90 mg/kg/day (approximately 1.4 times the maximum recommended human maintenance dose of 600 mg/day).

14 CLINICAL STUDIES

Apart from studies in patients with VT or VF, described below, there are two other studies of amiodarone showing an antiarrhythmic effect before significant levels of DEA could have accumulated. A placebo-controlled study of intravenous amiodarone (300 mg over 2 hours followed by 1200 mg/day) in post-coronary artery bypass graft patients with supraventricular and 2- to 3-consecutive-beat ventricular arrhythmias showed a reduction in arrhythmias from 12 hours on. A baseline-controlled study using a similar IV regimen in patients with recurrent, refractory VT/VF also showed rapid onset of antiarrhythmic activity; amiodarone therapy reduced episodes of VT by 85% compared to baseline.

The acute effectiveness of intravenous amiodarone in suppressing recurrent VF or hemodynamically unstable VT is supported by two randomized, parallel, dose-response studies of approximately 300 patients each. In these studies, patients with at least two episodes of VF or hemodynamically unstable VT in the preceding 24 hours were randomly assigned to receive doses of approximately 125 or 1000 mg over the first 24 hours, an 8-fold difference. In one study, a middle dose of approximately 500 mg was evaluated. The dose regimen consisted of an initial rapid loading infusion, followed by a slower 6-hour loading infusion, and then an 18-hour maintenance infusion. The maintenance infusion was continued up to hour 48. Additional 10-minute infusions of 150 mg intravenous amiodarone were given for "breakthrough" VT/VF more frequently to the 125 mg dose group, thereby considerably reducing the planned 8-fold differences in total dose to 1.8- and 2.6-fold, respectively, in the two studies.

The prospectively defined primary efficacy end point was the rate of VT/VF episodes per hour. For both studies, the median rate was 0.02 episodes per hour in patients receiving the high dose and 0.07 episodes per hour in patients receiving the low dose, or approximately 0.5 versus 1.7 episodes per day (p=0.07, 2-sided, in both studies). In one study, the time to first episode of VT/VF was significantly prolonged (approximately 10 hours in patients receiving the low dose and 14 hours in patients receiving the high dose). In both studies, significantly fewer supplemental infusions were given to patients in the high-dose group. At the end of double-blind therapy or after 48 hours, all patients were given open access to whatever treatment (including intravenous amiodarone) was deemed necessary. Mortality was not affected in these studies.

16 HOW SUPPLIED/STORAGE AND HANDLING

NEXTERONE (AMIODARONE HCI) PREMIXED INJECTION is supplied in the following dosage forms.
NDC 51662-4180-1
NEXTERONE (AMIODARONE HCI) PREMIXED INJECTION 150mg/100mL (1.5mg/mL) 100mL BAG

NDC 51662-4181-1
NEXTERONE (AMIODARONE HCI) PREMIXED INJECTION 360mg/200mL (1.8mg/mL) 200mL BAG

HF Acquisition Co LLC, DBA HealthFirst
Mukilteo, WA 98275

Also supplied in the following manufacture supplied dosage forms

NEXTERONE (amiodarone HCl) Premixed Injection is supplied as a ready-to-use, sterile, nonpyrogenic, iso-osmotic solution in 100 mL and 200 mL single-dose GALAXY containers (PL 2501 plastic) packaged in individual cartons as follows:

Do not add supplementary medication to NEXTERONE Premixed Injection.

Store at 20° - 25°C (68° - 77°F); excursions permitted to 15° - 30°C (59° - 86°F). See USP Controlled Room Temperature.

Protect from light and excessive heat. Protect from freezing.

Use carton to protect contents from light until used.

17 PATIENT COUNSELING INFORMATION

Amiodarone has the potential to cause serious side effects that limit its use to life-threatening and hemodynamically unstable cardiac arrhythmias. Advise female patients to discontinue nursing while being treated with amiodarone, as breast-feeding could expose the nursing infant to a significant dose of the drug. Recommend that patients avoid grapefruit juice, over-the-counter cough medicine (that commonly contain dextromethorphan), and St. John's Wort. Inform patients that most manufacturers of corneal refractive laser surgery devices contraindicate corneal refractive laser surgery in patients taking amiodarone. Discuss the symptoms of hypo- and hyper-thyroidism, particularly if patients will be transitioned to oral amiodarone.

SPL UNCLASSIFIED

Baxter, Galaxy and Nexterone are trademarks of Baxter International Inc.

Baxter Healthcare Corporation
Deerfield, IL 60015

07-19-77-918